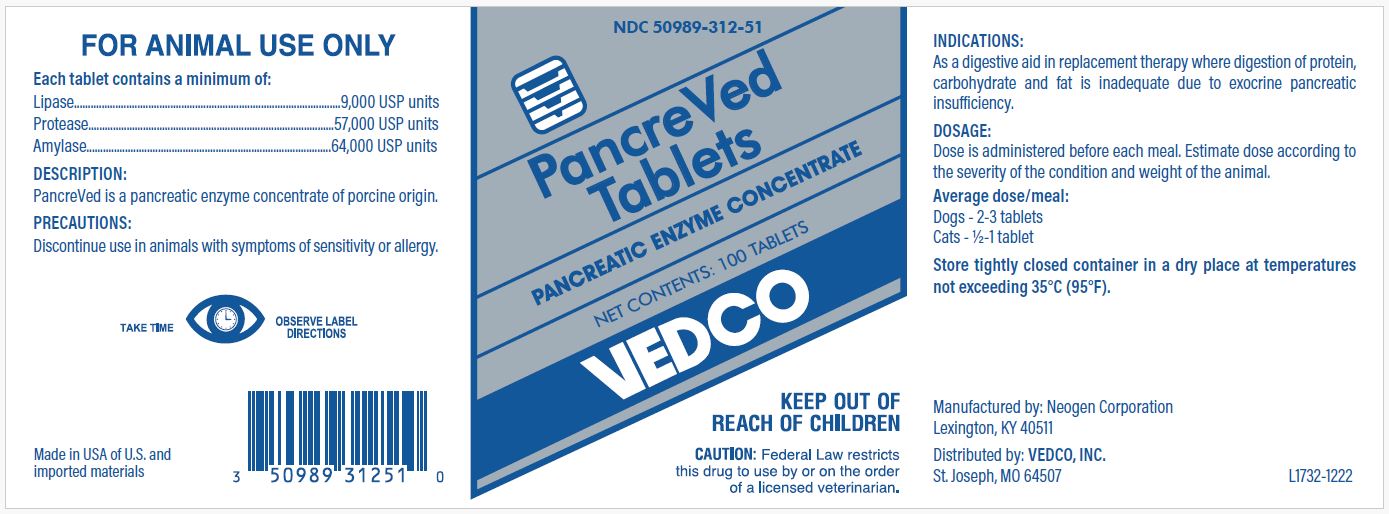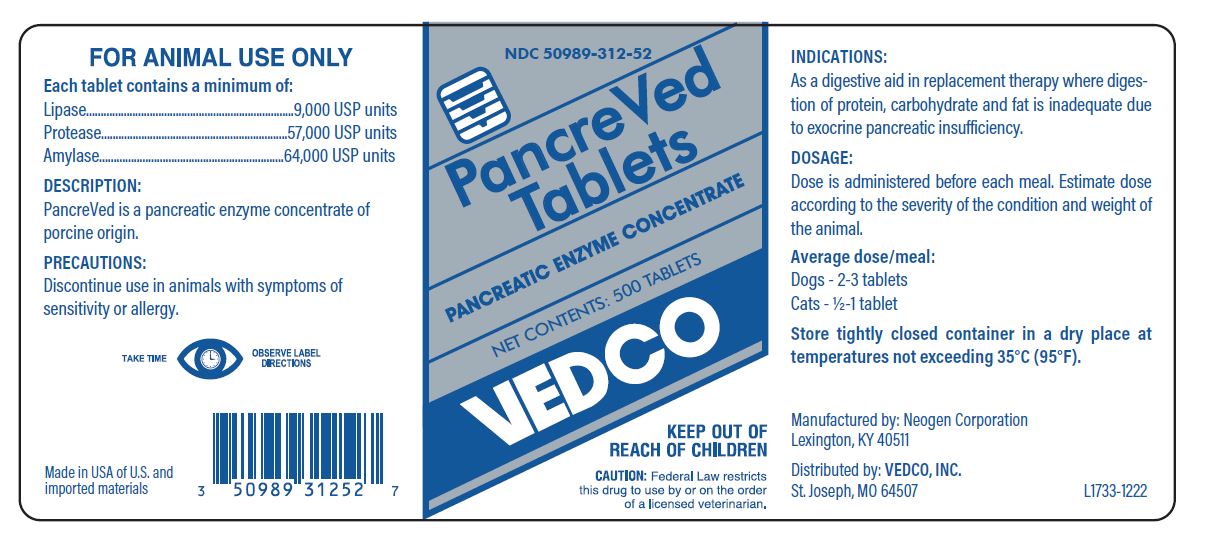 DRUG LABEL: PancreVed
NDC: 50989-312 | Form: Tablet
Manufacturer: Vedco, INC
Category: animal | Type: PRESCRIPTION ANIMAL DRUG LABEL
Date: 20240123

ACTIVE INGREDIENTS: PANCRELIPASE LIPASE 9000 [iU]/1 1; PANCRELIPASE AMYLASE 64000 [iU]/1 1; PANCRELIPASE PROTEASE 57000 [iU]/1 1

DESCRIPTION

PancreVed Tablets

PANCREATIC ENZYME CONCENTRATE

VEDCO

KEEP OUT OF REACH OF CHILDREN

CAUTION: Federal Law restricts this drug to use by or on the order of a licensed veterinarian.

Each tablet contains a minimum of:

Lipase.........................9,000 USP units

Protease...................57,000 USP units

Amylase....................64,000 USP units

DESCRIPTION:

PancreVed is a pancreatic enzyme concentrate of porcine origin.

TAKE TIME OBSERVE LABEL DIRECTIONS

Manufactured by Neogen Corporation

Lexington, KY 40511

Distributed by:

VEDCO, INC

St. Joseph, MO 64507

Made in USA of U.S. and imported materials

DOSAGE:

Dose is administered before each meal. Estimate dose according to the severity of the condition and weight of the animal.

Average dose/meal:

Dogs - 2 - 3 tablets

Cats - ½ - 1 tablet

INDICATIONS:

As a digestive aid in replacement therapy where digestion of protein, carbohydrate and fat is inadequate due to exocrine pancreatic insufficiency.

PRECAUTIONS:

Discontinue use in animals with symptoms of sensitivity or allergy.

PRINCIPAL DISPLAY PANEL - VEDCO PancreVed Tablets 100 Tablet Bottle

NDC 50989-312-51

PancreVed Tablets

PANCREATIC ENZYME CONCENTRATE

NET CONTENTS: 100 TABLETS

VEDCO

KEEP OUT OF REACH OF CHILDREN

CAUTION: Federal Law restricts this drug to use by or on the order of a licensed veterinarian.

PRINCIPAL DISPLAY PANEL - VEDCO PancreVed Tablets 500 Tablet Bottle

NDC 50989-312-52

PancreVed Tablets

PANCREATIC ENZYME CONCENTRATE

NET CONTENTS: 500 TABLETS

VEDCO

KEEP OUT OF REACH OF CHILDREN

CAUTION: Federal Law restricts this drug to use by or on the order of a licensed veterinarian.